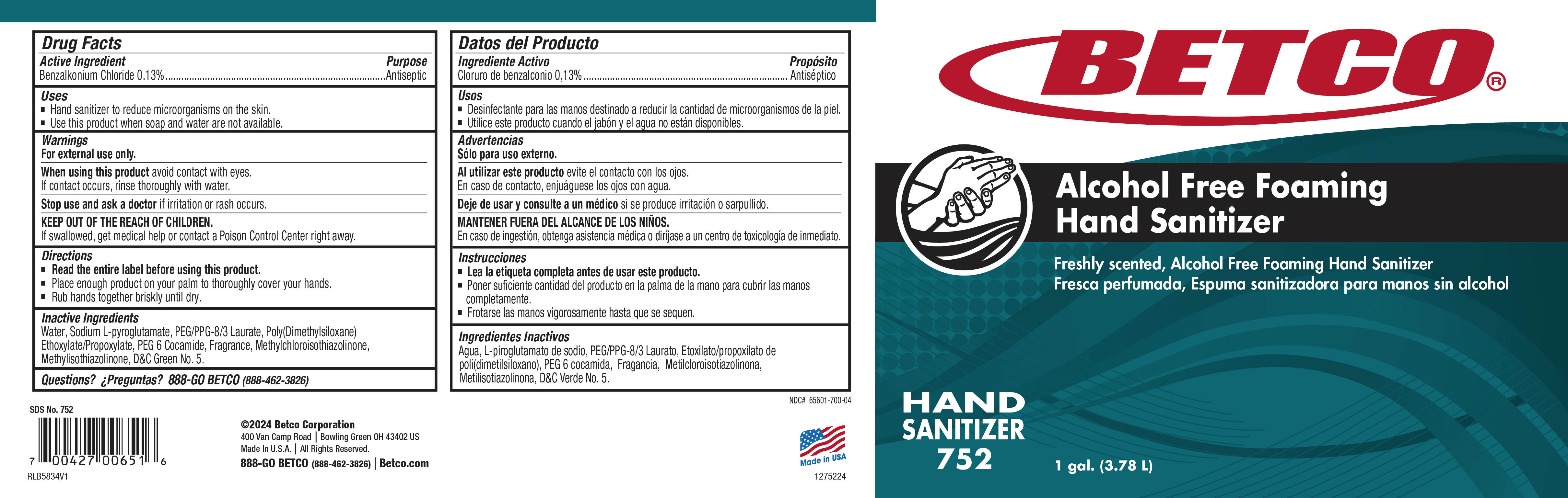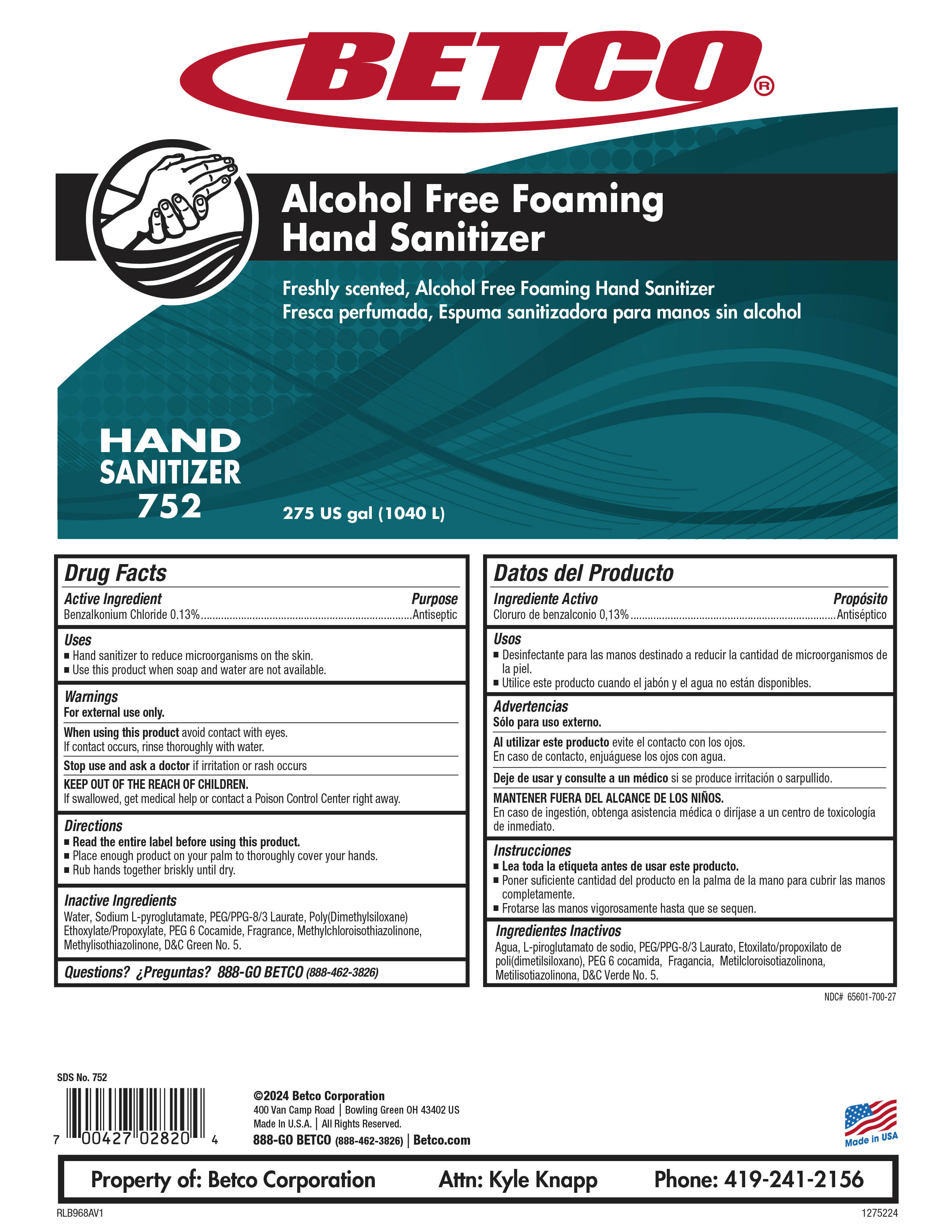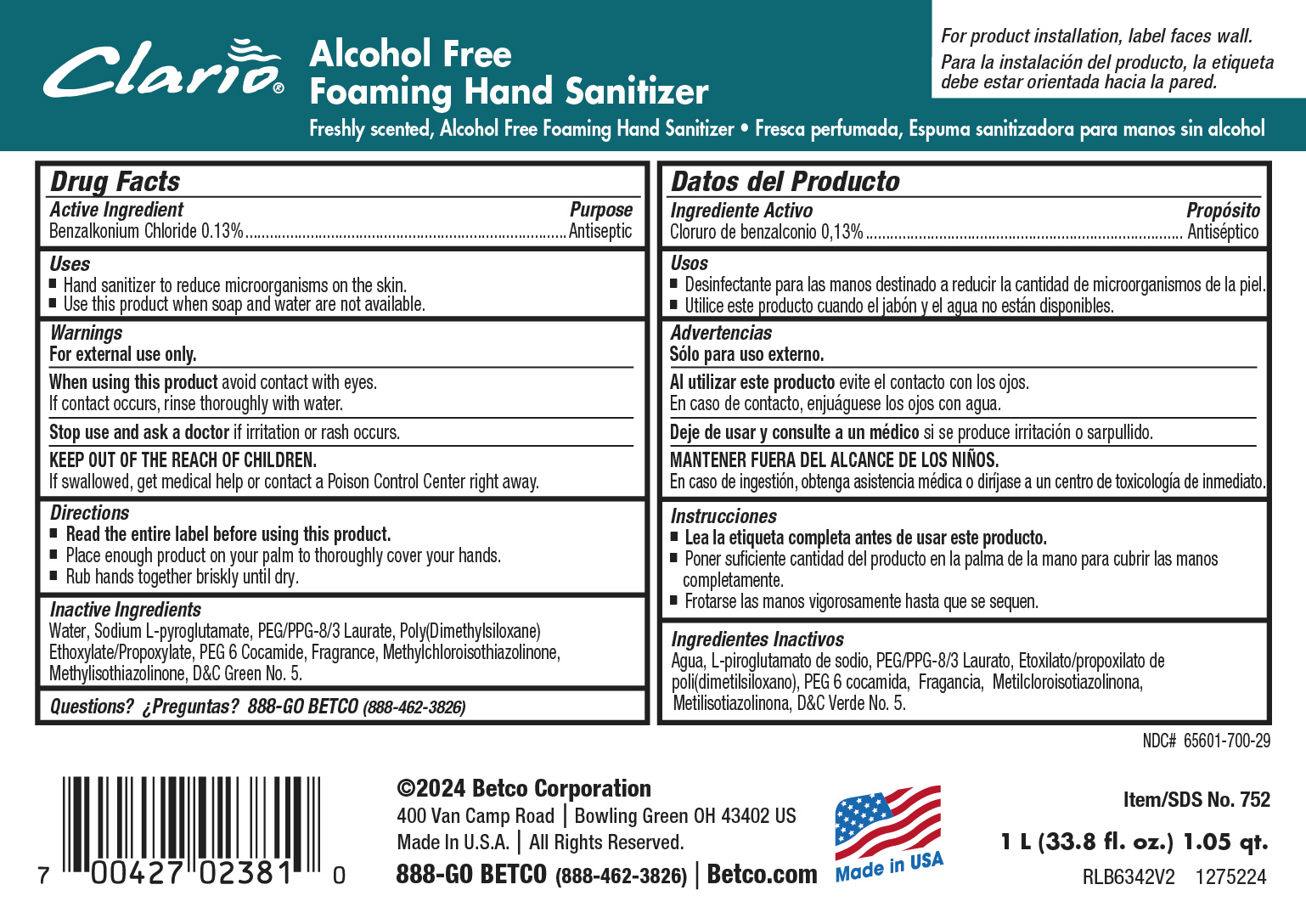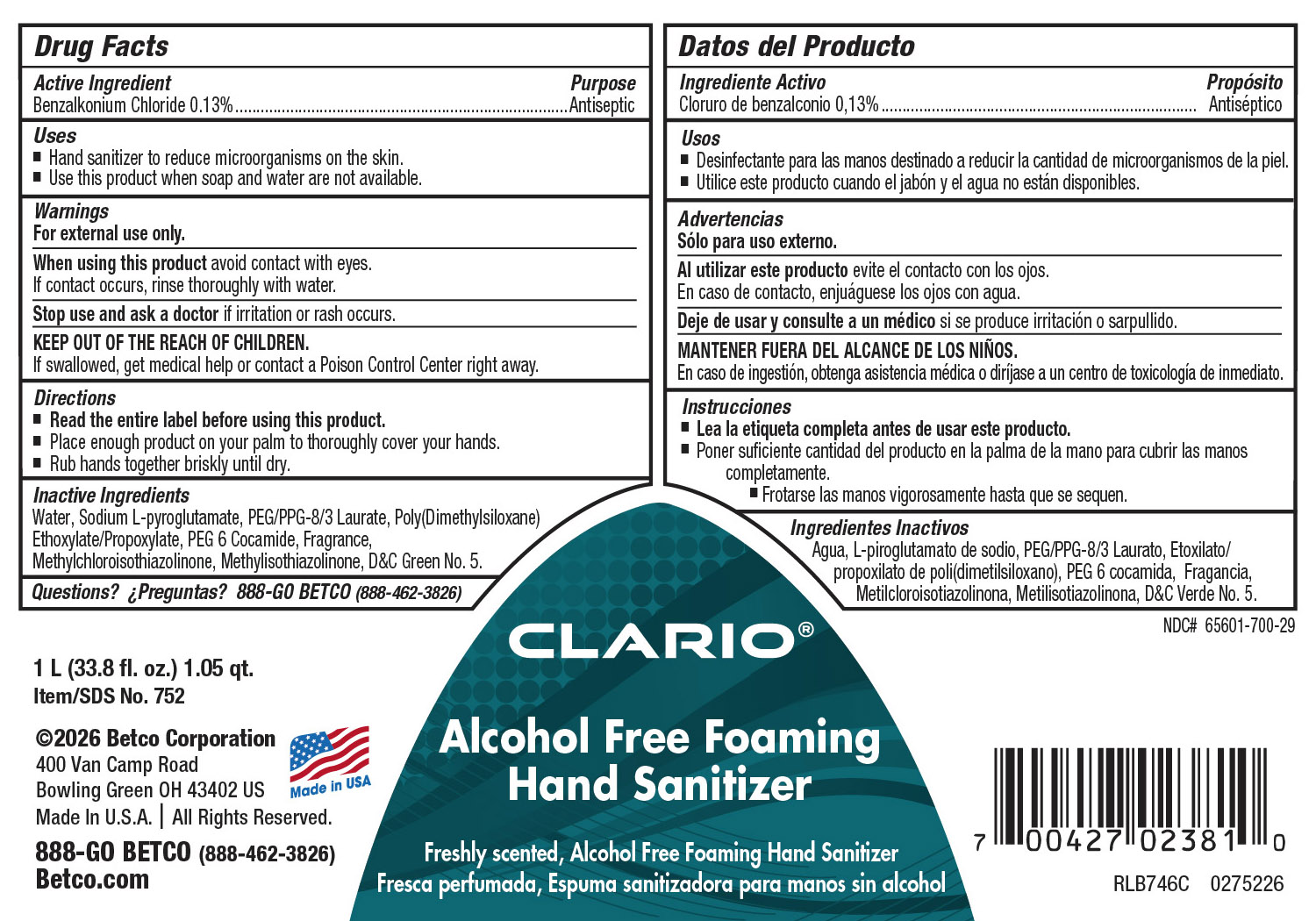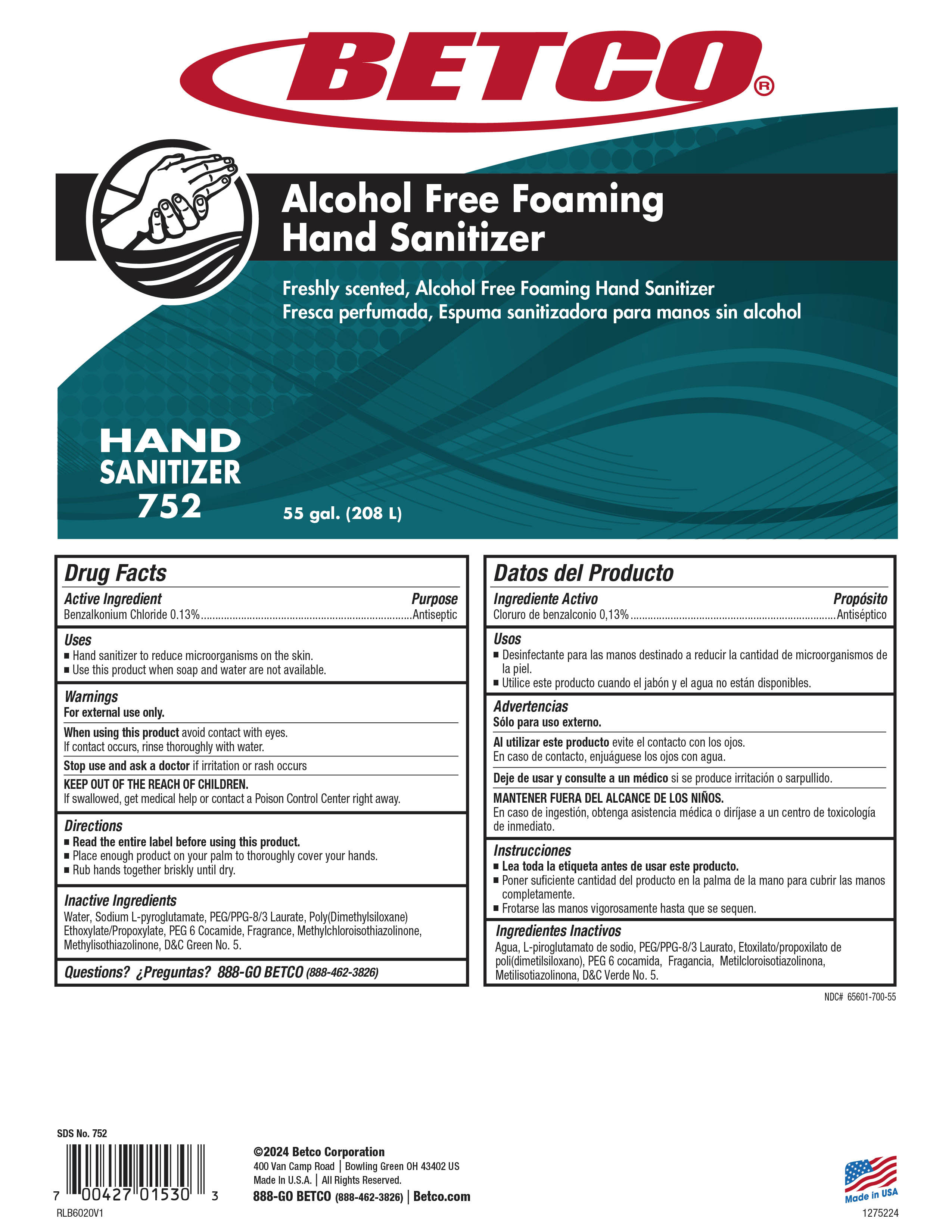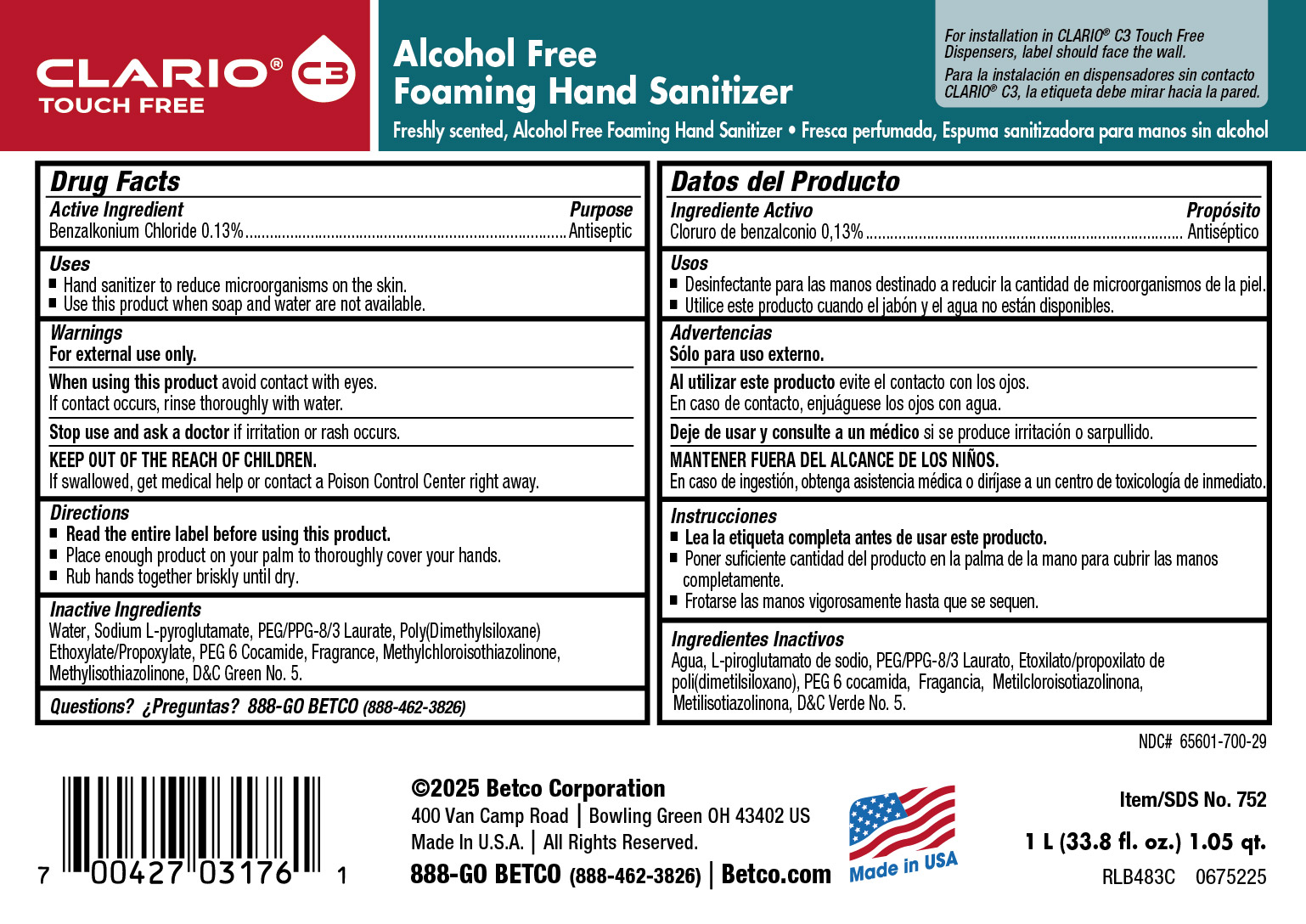 DRUG LABEL: Alcohol Free Foaming Hand Sanitizer
NDC: 65601-700 | Form: SOAP
Manufacturer: Betco Corporation, Ltd.
Category: otc | Type: HUMAN OTC DRUG LABEL
Date: 20260226

ACTIVE INGREDIENTS: BENZALKONIUM CHLORIDE 1.3 mg/1 mL
INACTIVE INGREDIENTS: .GAMMA.-TERPINENE; BUTYLPHENYL METHYLPROPIONAL; MAGNESIUM NITRATE; .BETA.-CITRONELLOL, (+/-)-; METHYLCHLOROISOTHIAZOLINONE; CYCLOMETHICONE 4; ACETALDEHYDE; GERANIOL; HEXAMETHYLINDANOPYRAN; METHYL DIHYDROJASMONATE (SYNTHETIC); ISOPROPYL ALCOHOL; N-ALKYL DIMETHYL BENZYL AMMONIUM CHLORIDE (C12-C18); LINALOOL, (+/-)-; D&C GREEN NO. 5; PEG/PPG-15/15 ALLYL ETHER ACETATE; HEXYL SALICYLATE; ALCOHOL; METHYLISOTHIAZOLINONE; WATER; PEG-6 COCAMIDE; .ALPHA.-PINENE; POLYETHYLENE GLYCOL 1000; NEROL; 2-METHYL-3-(P-METHOXYPHENYL)PROPANAL; LIMONENE, (+)-; HEXYL CINNAMAL; ALLYL CYCLOHEXANEPROPIONATE

Alcohol Free Foaming Hand Sanitizer

Alcohol Free Foaming Hand Sanitizer

Active Ingredient

Benzalkonium Chloride 0.13%

Alcohol Free Foaming Hand Sanitizer

Uses

- Hand sanitizer to remove microorganisms on the skin.
- Use this product when soap and water are not available.

Alcohol Free Foaming Hand Sanitizer

Warnings

- For external use only.
- Avoid contact with eyes. If contact occurs, rinse thoroughly with water.
- Discontinue use is irritation or redness develops.
- If irritation persists for more than 72 hours, consult a physician.
- KEEP OUT OF REACH OF CHILDREN.
- If swallowed, get medical help or contact a Poison Control Center right away.

Alcohol Free Foaming Hand Sanitizer

Directions

- Read the entire label before using this product.
- Dispense 2 pumps of product onto palm of hand and rub thoroughly over all surfaces of both hands until dry.

Alcohol Free Foaming Hand Sanitizer

Inactive Ingredients

Deionized Water, Sodium PCA, PEG/PPG-8/3 Laurate, Dimethicone, PEG-3 Cocamide, Fragrance, Methyl Chloro Isothiazolinone, Methyl Isothiazolinone, D&C Green #5.

Alcohol Free Foaming Hand Sanitizer

Questions or Comments? Phone: (800) 777-9343

MDS information:(800) 891-4965

Alcohol Free Foaming Hand Sanitizer

Purpose

Antiseptic

Alcohol Free Foaming Hand Sanitizer

KEEP OUT OF REACH OF CHILDREN